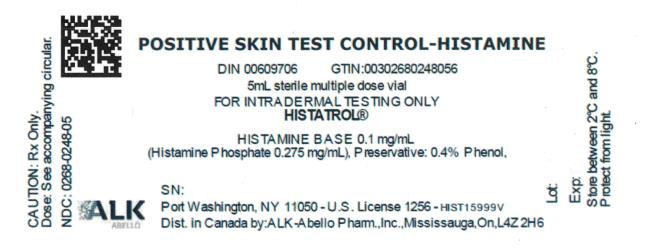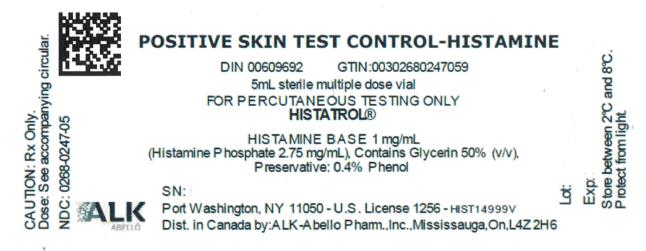 DRUG LABEL: histamine positive
NDC: 0268-0248 | Form: INJECTION, SOLUTION
Manufacturer: ALK-Abello, Inc.
Category: prescription | Type: HUMAN PRESCRIPTION DRUG LABEL
Date: 20200828

ACTIVE INGREDIENTS: HISTAMINE PHOSPHATE 0.275 mg/1 mL
INACTIVE INGREDIENTS: PHENOL 0.004 mL/1 mL; HYDROCHLORIC ACID; SODIUM HYDROXIDE

Histamine Phosphate

Directions for Use of
Positive Skin Test Control - Histamine
HISTATROL®

Histamine Base 1 mg/mL
(Histamine Phosphate 2.75 mg/mL)
in Glycerin 50% (v/v)
For Percutaneous Testing

Histamine Base 0.1 mg/mL
(Histamine Phosphate 0.275 mg/mL)
For Intracutaneous (Intradermal) Testing

Port Washington, New York 11050

U.S. Government License No. 1256

DESCRIPTION

The chemical formula for Histamine Phosphate is C5H9 N3 · 2H3 PO4; its molecular weight is 307.14. For prick, puncture or scratch testing, the product is a sterile solution that contains 1 mg/mL histamine base (2.75 mg/mL Histamine Phosphate) in Water for Injection; it also contains Glycerin 50% (v/v) as viscosity agent and Phenol 0.4% as preservative. For intracutaneous (intradermal) skin testing, the product is a sterile solution that contains 0.1 mg/mL histamine base (0.275 mg/mL Histamine Phosphate) in Water for Injection and Phenol 0.4% as preservative. The product should be stored refrigerated and protected from light.

CLINICAL PHARMACOLOGY

Histamine acts as a potent vasodilator when released from mast cells during an allergic reaction. It is largely responsible for the immediate skin test reaction of a sensitive patient when challenged with an offending allergen.

The effect of added Glycerin (50% v/v) to 1 mg/mL histamine base was studied by puncture testing using a bifurcated needle in twelve volunteer subjects. The mean sum of cross-diameters of the wheals was 13.25 mm (range 10-15 mm) for the non-glycerinated, and 12.54 mm (range 9-15 mm) for the glycerinated formulation. Sum of cross-diameters of erythema was 52.88 mm (range 23-92 mm) for the non-glycerinated, and 54.42 mm (range 19-87 mm) for the glycerinated formulation. These differences are not statistically significant.

INDICATIONS AND USAGE

For use as a positive control in evaluation of allergenic (immediate hypersensitivity or "Type I") skin testing.

CONTRAINDICATIONS

Histamine should not be injected into individuals with hypotension, severe hypertension, severe cardiac, pulmonary, or renal disease. Not to be used for diagnosis of pheochromocytoma or to test the ability of the gastric mucosa to secrete hydrochloric acid.

WARNINGS

Care must be taken in intracutaneous testing to avoid injection into a venule or capillary. Pull back gently on the syringe plunger and note if blood is drawn. If blood is drawn, withdraw needle and inject into another skin site.

Small doses by any route of administration may precipitate asthma in patients with bronchial hyperactivity. This product is not intended for inhalation, or subcutaneous injection. The utmost caution is advised in using histamine in such patients and in those with a history of bronchial asthma.

PRECAUTIONS

General

A separate sterile needle or other percutaneous testing device should be used for each individual patient to prevent transmission of hepatitis and other infectious agents from one person to another.

Epinephrine Injection (1:1,000) and injectable antihistamines should be available for immediate use in the event the patient exhibits a severe response. A tourniquet can be applied above the test site to slow absorption if a severe response occurs.

Drug Interactions

Drugs can interfere with the performance of skin tests in general, and specifically with histamine^1.

Antihistamines: Response to histamine is suppressed by antihistamines. The length of suppression varies, and is dependent on individual patient, type of antihistamine and length of time the patient has been on antihistamines. The duration of this suppression may be as little as 24 hours (chlorpheniramine), and can be as long as 40 days (astemizole).

Tricyclic Antidepressants: These exert a potent and sustained decrease of skin reactivity to histamine, which may last for a few weeks.

Beta2 Agonists: Oral terbutaline and parenteral ephedrine, in general, have been shown to decrease allergen induced wheal. Theoretically, this may also reduce whealing capacity to histamine.

Dopamine: Intravenous infusion of dopamine has been shown to inhibit skin test responses to histamine.

Beta Blocking Agents: Propranolol can significantly increase skin test reactivity, including histamine.

Other Drugs: Short acting steroids, inhaled beta agonists, theophylline and cromolyn do not seem to affect skin test response.

Carcinogenesis, Mutagenesis, Impairment of Fertility

Animal studies have not been conducted with Histamine.

Nursing Mothers

It is not known if Histamine administered percutaneously or intracutaneously appears in human milk. Because many drugs are excreted in human milk, caution should be exercised when histamine is administered to a nursing woman.

Pregnancy Category C

It is not known whether Histamine can cause fetal harm when administered during pregnancy or whether it can affect reproduction capacity. Histamine should be given during pregnancy only if clearly needed.

There are no adequate and well-controlled studies during pregnancy. However, based on histamine's known ability to contract uterine muscle, exposure or repeated doses should be avoided.

HISTATROL® should be used during pregnancy only if the potential benefit justifies the potential risk to the fetus or mother.

Pediatric Use

Histamine solutions for percutaneous testing have been given safely in infants and young children.^2,3,4,5 Neonates and infants have lower skin test reactivity to histamines as well as common allergens.^3,4,5,6 About 20% of infants less than six months of age have been observed to have a negative reaction to histamine hydrochloride (1 mg/mL of salt).^4 Skin test reactivity gradually increases to age six and plateaus to age sixty.^2,3 Therefore, small skin test reactions should be anticipated in children under age six.

ADVERSE REACTIONS

Local:

Reactions such as wheal, erythema and localized pruritus are to be expected, but if very large (i.e. greater than 4+ as described dosage and administration) may be the first manifestation of a systemic reaction.

Systemic:

Following the injection of large doses of histamine, systemic reactions may include flushing, dizziness, headache, bronchial constriction, urticaria, asthma, marked hypertension or hypotension, abdominal cramps, vomiting, metallic taste, and local or generalized allergic manifestations (see also OVERDOSAGE).

OVERDOSAGE

A large subcutaneous dose of Histamine Phosphate may cause severe occipital headache, blurred vision, anginal pain, a rapid drop in blood pressure, and cyanosis of the face. Overdosage may cause severe symptoms including vasomotor collapse, shock, and even death.

Epinephrine Injection 0.01 mg/kg to a maximum of 1.0 mg given subcutaneously or intramuscularly should be used in case of emergency due to severe reactions (see Precautions). An antihistamine preparation may be given intramuscularly to ameliorate systemic reaction to overdose.

DOSAGE AND ADMINISTRATION

Parenteral drug products should be inspected visually for particulate matter and discoloration prior to administration, whenever solution and container permit.

For Prick, Puncture and Scratch Testing

Histamine base 1 mg/mL (Histamine Phosphate 2.75 mg/mL) should be used to give a reaction. (Refer to Interpretation Section.)

Prick, Puncture or Scratch Test Techniques

1. The skin in the test area should be cleansed with alcohol and air dried.
2. The histamine control skin test solution should be placed at the same site with the other skin test antigens, either on the patient's back or on the volar surface of the forearm. The patient should be placed in a comfortable position before the testing is begun.
3. For the prick test, a sharp needle is used to puncture the skin, but not to draw blood. If the scratch test is used, carefully break or scratch the skin with a sterile scarifier. Do not draw blood. Each scratch should be about 2 mm - 4 mm in length.
4. A small drop of the histamine base 1 mg/mL (Histamine Phosphate 2.75 mg/mL) is placed on the abraded skin site no closer than 4 or 5 cm from an adjacent test site. Some physicians prefer to place the solution on the test area and then prick through the drop with a sharp needle.
5. Use a separate sterile scarifier or needle for each patient.
6. The test should be read at 15 minutes; if a large wheal reaction occurs before that time the test site should be wiped free of histamine.

Interpretation

The patient's response is based on the size of: erythema (degree of redness) and/or size of wheal (smooth, slightly elevated area) which appear after 10 minutes.

For percutaneous testing, different devices and/or techniques influence the size of the reaction. Therefore, it is important to refer to the device manufacturer's or distributor's instructions when grading reactions.

For prick, puncture and scratch testing, histamine base 1 mg/mL (Histamine Phosphate 2.75 mg/mL) should be used to give a positive reaction. In a large population, the NHANES II survey reports a mean diameter (average of length and width) wheal of 4.4 mm ± 1.65 mm (± standard deviation) and a mean erythema of 18.4 mm ± 8.55 mm (± standard deviation) when using 25 gauge B-D needle by prick puncture (Pepys) technique.^7 All positive reactions should be interpreted against an appropriate negative control.

For Intradermal Skin Testing

Histamine base 0.1 mg/mL (Histamine Phosphate 0.275 mg/mL) or 0.01 mg/mL should be used to give a reaction. (Refer to Interpretation Section.)

Intracutaneously (Intradermal) Test Techniques

1. The skin should be cleansed with alcohol and air dried.
2. A sterile one milliliter tuberculin syringe with 26 or 27 gauge needle should be used. A single sterile syringe should be used for each solution to assure sterility. Only the histamine base 0.1 mg/mL (Histamine Phosphate, 0.275 mg/mL) or greater dilution solution should be used.
3. The histamine base skin test solution should be injected at the same site with the other skin test allergens, either on the patient's back or on the arm. The patient should be placed in a comfortable position before the testing is begun.
4. The skin is held tense and the needle is inserted almost parallel to the skin, bevel side up, far enough to cover the beveled portion. Slowly inject 0.01 mL or 0.02 mL, making a small bleb approximately 3 mm - 5 mm in diameter.
5. The test should be read in 15 minutes.

Interpretation

The patient's response is based on the size of: erythema (degree of redness) and/or size of wheal (smooth, slightly elevated area) which appear after 10 minutes.

For intradermal skin testing, histamine base 0.1 mg/mL (Histamine Phosphate 0.275 mg/mL) or 0.01 mg/mL should be used to give a positive reaction. The available 0.1 mg/mL concentration must be diluted ten-fold to achieve this dose. All positive reactions should be interpreted against an appropriate negative control. In two successive years of testing, the Committee on Standardization of the American College of Allergy reported positive reactions at histamine base doses of 0.01 mg/mL and higher. Mean sum of wheal diameters was approximately 14 mm ± 4.8 mm and sum of erythema diameter was approximately 52 mm ± 21.6 mm following 0.01 mL intradermal doses of 0.01 mg/mL histamine base. When 0.01 mL of 0.1 mg/mL histamine base was injected, the sum of cross-diameters of wheal ranged from 15-20 mm and the sum of cross-diameters of erythema ranged from 60-80 mm.^8

HOW SUPPLIED

Multidose vials containing 5 mL histamine base, 1 mg/mL (Histamine Phosphate 2.75 mg/mL) in Glycerin 50% (v/v) for prick, puncture, or scratch testing. Multidose vials containing 5 mL histamine base, 0.1 mg/mL (Histamine Phosphate 0.275 mg/mL) in aqueous solution for intradermal testing. Store at 2° - 8°C.

REFERENCES

1. Bousquet, J.: In vivo methods for the study of allergy: skin test, techniques, and interpretation. In Allergy Principles and Practice, 3rd Edition, Middleton, et al eds., C.V. Mosby, St. Louis, MO, 1988.
2. Skassa-Brociek, W., et al: Skin test reactivity to histamine from infancy to old age. J. Allergy Clin. Immunol. 80:711, 1987.
3. Menardo, J.L., et al: Skin test reactivity in infancy. J. Allergy Clin. Immunol. 75:646, 1985.
4. Van Asperen, P.P., et al: Skin test reactivity and clinical allergen sensitivity in infancy. J. Allergy Clin. Immunol. 73:381, 1984.
5. Matheson, A., et al: Reactivity of the skin of the newborn infant. Pediatrics 10:181, 1952.
6. Stevenson, D.D., et al: Development of IgE in newborn human infants. J. Allergy 48:61, 1971.
7. National Center for Health Statistics, P.J. Gergen and P.C. Turkeltaub: Percutaneous immediate hypersensitivity to eight allergens, United States, 1976-80. Vital and Health Statistics. Series 11, No. 235. DHHS Pub. No. (PHS) 86-1685. Public Health Service. Washington. U.S. Government Printing Office, July 1986.
8. Committee on Standardization. Report of the Committee on Standardization: 1. A method of evaluating skin test response. Ann. Allergy 29:30-34, 1971.

Revision: October 2008

© Alk-Abello, Inc., 2008 No. 107K

Distributed in Canada by:
ALK-Abelló Pharmaceuticals, Inc.
#35-151 Brunel Road
Mississauga, Ontario
Canada L4Z 2H6

PRINCIPAL DISPLAY PANEL

POSITIVE SKIN TEST CONTROL-HISTAMINE
5mL sterile multiple dose vial
FOR INTRADERMAL TESTING ONLY
HISTATROL®
HISTAMINE BASE 0.1 mg/mL

PRINCIPAL DISPLAY PANEL

POSITIVE SKIN TEST CONTROL-HISTAMINE
5mL sterile multiple dose vial
FOR PERCUTANEOUS TESTING ONLY
HISTATROL®
HISTAMINE BASE 1 mg/mL